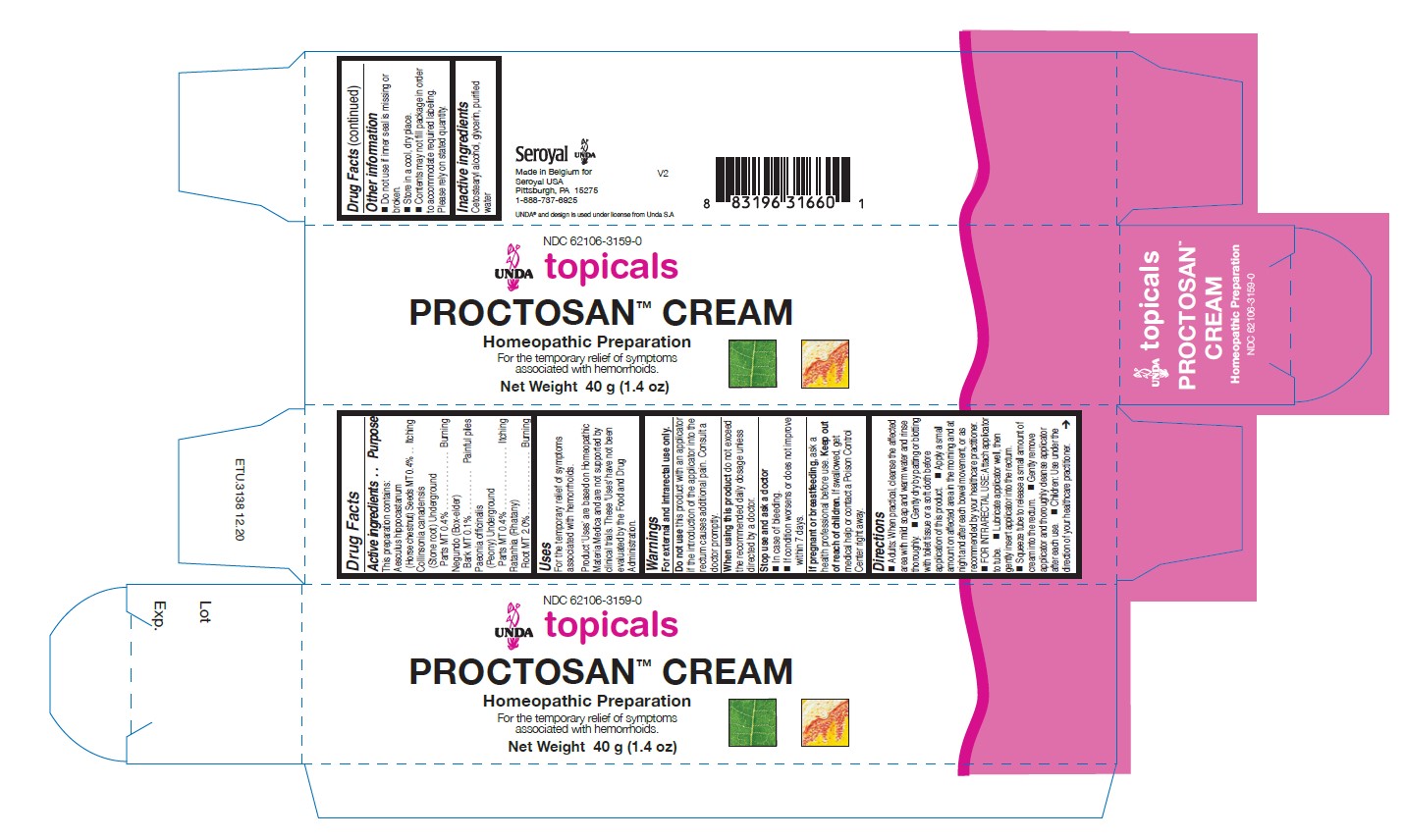 DRUG LABEL: Proctosan Cream
NDC: 62106-3159 | Form: CREAM
Manufacturer: Seroyal USA
Category: homeopathic | Type: HUMAN OTC DRUG LABEL
Date: 20210714

ACTIVE INGREDIENTS: KRAMERIA LAPPACEA ROOT 1 [hp_X]/40 g; COLLINSONIA CANADENSIS ROOT 1 [hp_X]/40 g; PAEONIA OFFICINALIS ROOT 1 [hp_X]/40 g; HORSE CHESTNUT 1 [hp_X]/40 g; ACER NEGUNDO INNER BARK 1 [hp_X]/40 g
INACTIVE INGREDIENTS: WATER; GLYCERIN; CETOSTEARYL ALCOHOL

PROCTOSAN CREAM

Active ingredients
This preparation contains:
Aesculus hippocastanum (Horse chestnut) Seeds MT 0.4%
Collinsonia canadensis (Stone root) Underground Parts MT 0.4%
Negundo (Box-elder) Bark MT 0.1%
Paeonia officinalis (Peony) Underground Parts MT 0.4%
Ratanhia (Rhatany) Root MT 2.0%

Uses
For the temporary relief of symptoms associated with hemorrhoids.

Warnings
For external and intrarectal use only.

Do not use this product with an applicator if the introduction of the applicator into the
rectum causes additional pain. Consult a doctor promptly.

When using this product do not exceed the recommended daily dosage unless directed by a doctor.

Stop use and ask a doctor
In case of bleeding.
If condition worsens or does not improve within 7 days.

If pregnant or breastfeeding, ask a health professional before use.

Keep out of reach of children. If swallowed, get medical help or

contact a Poison Control Center right away.

Keep out of reach of children.

OVERDOSAGE

If swallowed, get medical help or contact a Poison Control Center right away.

Other information
Do not use if inner seal is missing or broken.
Store in a cool, dry place.

Contents may not fill package in order
to accommodate required labeling.
Please rely on stated quantity.

Inactive ingredients
Cetostearyl alcohol, glycerin, purified water

Directions
Adults: When practical, cleanse the affected
area with mild soap and warm water and rinse
thoroughly. Gently dry by patting or blotting
with toilet tissue or a soft cloth before
application of this product. Apply a small
amount on affected area in the morning and at
night and after each bowel movement, or as
recommended by your healthcare practitioner.
FOR INTRARECTAL USE: Attach applicator
to tube. Lubricate applicator well, then gently
insert applicator into the rectum. Squeeze
tube to release a small amount of cream into
the rectum. Gently remove applicator and
thoroughly cleanse applicator after each use.
Children: Use under the direction of your
healthcare practitioner.

Uses
For the temporary relief of symptoms associated with hemorrhoids.

Directions
Adults: When practical, cleanse the affected
area with mild soap and warm water and rinse
thoroughly. Gently dry by patting or blotting
with toilet tissue or a soft cloth before
application of this product. Apply a small
amount on affected area in the morning and at
night and after each bowel movement, or as
recommended by your healthcare practitioner.
FOR INTRARECTAL USE: Attach applicator
to tube. Lubricate applicator well, then gently
insert applicator into the rectum. Squeeze
tube to release a small amount of cream into
the rectum. Gently remove applicator and
thoroughly cleanse applicator after each use.
Children: Use under the direction of your
healthcare practitioner.

PACKAGE LABEL

NDC 62106-3159-0

UNDA topicals

PROCTOSAN CREAM

Homeopathic Preparation

For the temporary relief of symptoms
associated with hemorrhoids.

Net Weight 1.4 oz (40 g)